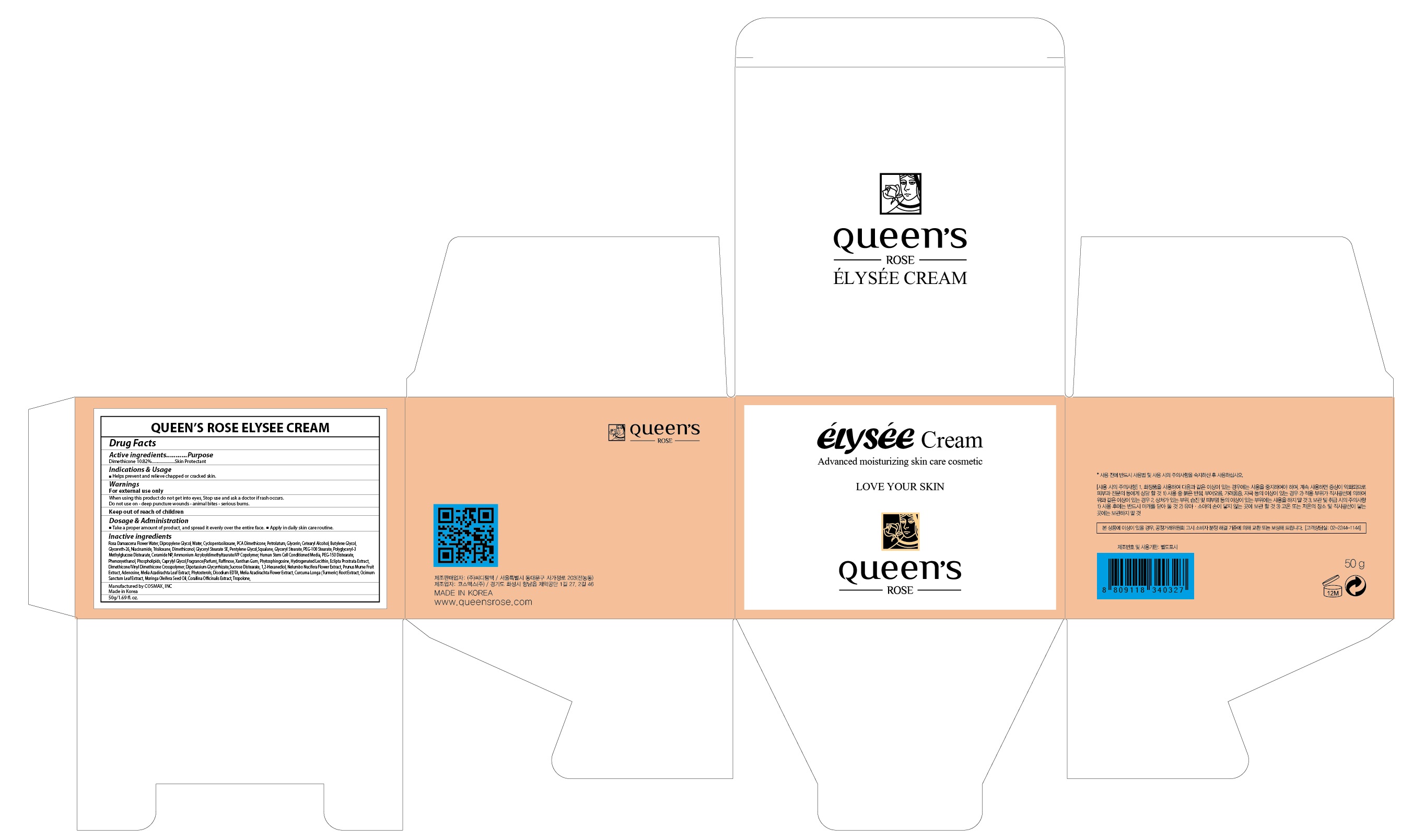 DRUG LABEL: QUEENS ROSE ELYSEE
NDC: 71252-080 | Form: CREAM
Manufacturer: Cdpharmtec Co.,ltd
Category: otc | Type: HUMAN OTC DRUG LABEL
Date: 20170324

ACTIVE INGREDIENTS: Dimethicone 5.41 g/50 g
INACTIVE INGREDIENTS: ROSA DAMASCENA FLOWER OIL; Dipropylene Glycol

ACTIVE INGREDIENT

Active ingredients: Dimethicone 10.82%

INACTIVE INGREDIENT

Inactive ingredients: Rosa Damascena Flower Water, Dipropylene Glycol, Water, Cyclopentasiloxane, PCA Dimethicone, Petrolatum, Glycerin, Cetearyl Alcohol, Butylene Glycol, Glycereth-26, Niacinamide, Trisiloxane, Dimethiconol, Glyceryl Stearate SE, Pentylene Glycol,Squalane, Glyceryl Stearate, PEG-100 Stearate, Polyglyceryl-3 Methylglucose Distearate, Ceramide NP, Ammonium Acryloyldimethyltaurate/VP Copolymer, Human Stem Cell Conditioned Media, PEG-150 Distearate, Phenoxyethanol, Phospholipids, Caprylyl Glycol,Fragrance(Parfum), Raffinose, Xanthan Gum, Phytosphingosine, Hydrogenated Lecithin, Eclipta Prostrata Extract, Dimethicone/Vinyl Dimethicone Crosspolymer, Dipotassium Glycyrrhizate,Sucrose Distearate, 1,2-Hexanediol, Nelumbo Nucifera Flower Extract, Prunus Mume Fruit Extract, Adenosine, Melia Azadirachta Leaf Extract, Phytosterols, Disodium EDTA, Melia Azadirachta Flower Extract, Curcuma Longa (Turmeric) Root Extract, Ocimum Sanctum Leaf Extract, Moringa Oleifera Seed Oil, Corallina Officinalis Extract, Tropolone,

PURPOSE

Purpose: Skin Protectant

WARNINGS

Warnings: For external use only When using this product do not get into eyes, Stop use and ask a doctor if rash occurs. Do not use on - deep puncture wounds - animal bites - serious burns.

KEEP OUT OF REACH OF CHILDREN

INDICATIONS & USAGE

Indications & Usage: Helps prevent and relieve chapped or cracked skin.

DOSAGE & ADMINISTRATION

Dosage & Administration: - Take a proper amount of product, and spread it evenly over the entire face. - Apply in daily skin care routine.